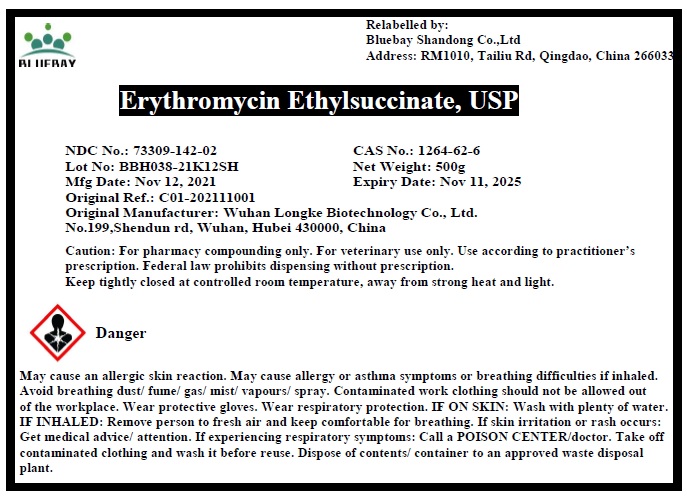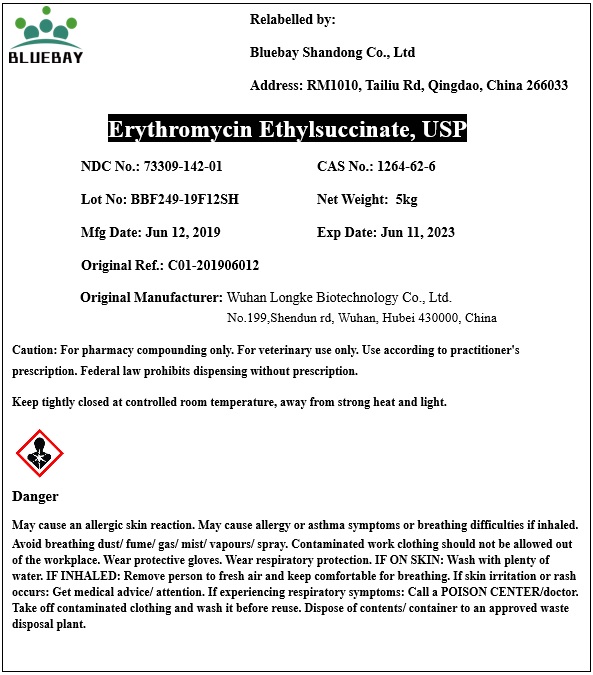 DRUG LABEL: Erythromycin Ethylsuccinate
NDC: 73309-142 | Form: POWDER
Manufacturer: BLUEBAY SHANDONG CO.,LTD
Category: other | Type: BULK INGREDIENT - ANIMAL DRUG
Date: 20220307

ACTIVE INGREDIENTS: ERYTHROMYCIN ETHYLSUCCINATE 1 kg/1 kg

Erythromycin Ethylsuccinate